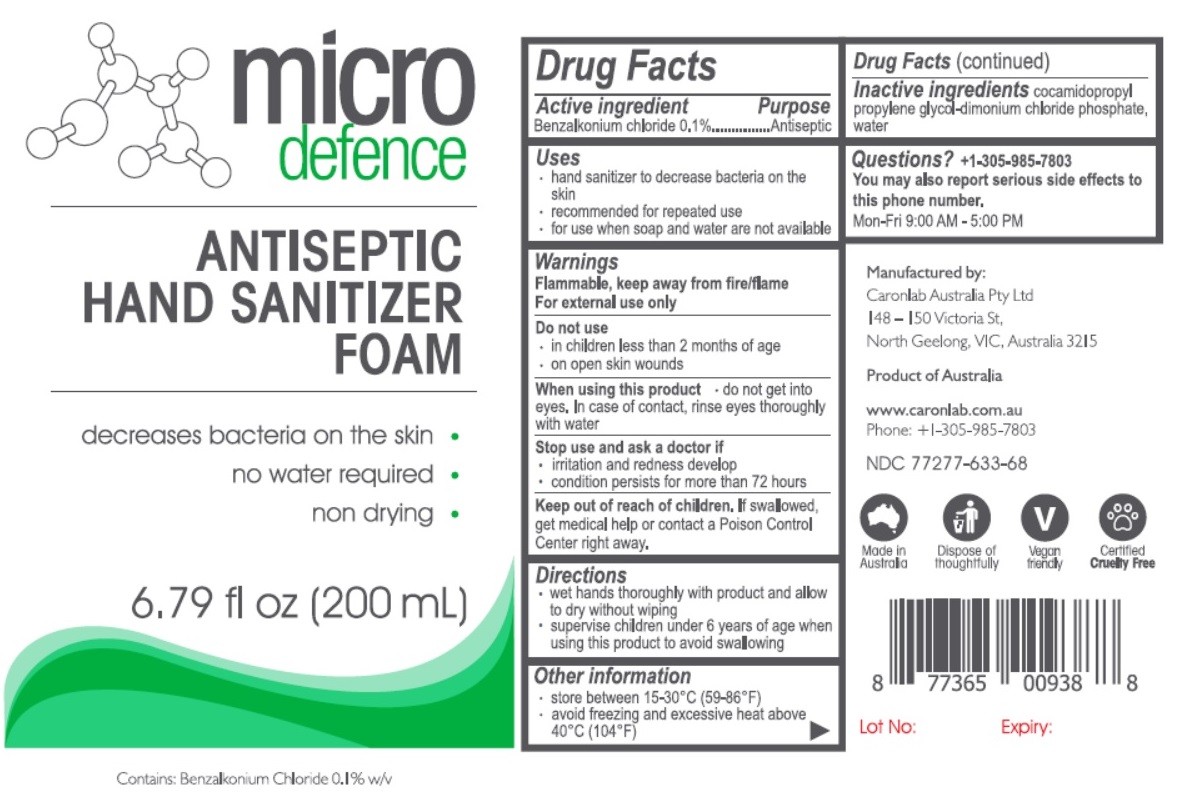 DRUG LABEL: MICRO DEFENCE ANTISEPTIC HAND SANITIZER FOAM
NDC: 77277-633 | Form: LIQUID
Manufacturer: CARONLAB AUSTRALIA PTY LTD
Category: otc | Type: HUMAN OTC DRUG LABEL
Date: 20220119

ACTIVE INGREDIENTS: BENZALKONIUM CHLORIDE 0.1 g/100 mL
INACTIVE INGREDIENTS: COCAMIDOPROPYL PROPYLENE GLYCOL-DIMONIUM CHLORIDE PHOSPHATE; WATER

micro defence ANTISEPTIC HAND SANITIZER FOAM

Active ingredient

Benzalkonium chloride 0.1%

Purpose

Antiseptic

Uses

- hand sanitizer to decrease bacteria on the skin
- recommended for repeated use
- for use when soap and water are not available

Warnings

Flammable, keep away from fire/flame

For external use only

Do not use

- in children less than 2 months of age
- on open skin wounds

When using this product • do not get into eyes. In case of contact, rinse eyes thoroughly with water

Stop use and ask a doctor if

- irritation and redness develop
- condition persists for more than 72 hours

Keep out of reach of children. If swallowed, get medical help or contact a Poison Control Center right away

Directions

- wet hands thoroughly with product and allow to dry without wiping
- supervise children under 6 years of age when using this product to avoid swallowing

Other information

- store between 15-30°C (59-86°F)
- avoid freezing and excessive heat above 40°C (104°F)

INACTIVE INGREDIENT

Inactive ingredients cocamidopropyl propylene glycol-dimonium chloride phosphate, water

Questions? +1-305-985-7803
You may also report serious side effects to this phone number.
Mon-Fri 9:00 AM - 5:00 PM

- decreases bacteria on the skin
- no water required
- non drying

Contains: Benzalkonium Chloride 0.1% w/v

Manufactured by:

Caronlab Australia Pty Ltd

148-150 Victoria St,

North Geelong, VIC, Australia 3215

Product of Australia

www.caronlab.com.au

Phone: + 1-305-985-7803

Made in Australia Dispose of thoughtfully Vegan friendly Certified Cruelty Free